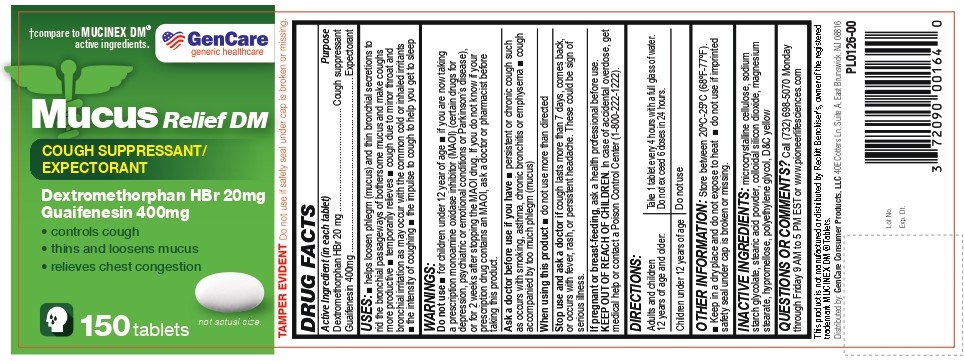 DRUG LABEL: Mucus Relief DM
NDC: 72090-027 | Form: TABLET
Manufacturer: Pioneer Life Sciences, LLC
Category: otc | Type: HUMAN OTC DRUG LABEL
Date: 20251226

ACTIVE INGREDIENTS: DEXTROMETHORPHAN HYDROBROMIDE 20 mg/1 1; GUAIFENESIN 400 mg/1 1
INACTIVE INGREDIENTS: microcrystalline cellulose; SODIUM STARCH GLYCOLATE TYPE A; STEARIC ACID; SILICON DIOXIDE; MAGNESIUM STEARATE; HYPROMELLOSE, UNSPECIFIED; POLYETHYLENE GLYCOL, UNSPECIFIED; D&C YELLOW NO. 10 ALUMINUM LAKE

Mucus Relief DM

Active Ingredient (in each tablet)

Dextromethorphan HBr 20 mg

Guaifenesin 400mg

Purpose

Dextromethorphan HBr 20 mg ......................................... Cough suppressant
Guaifenesin 400mg ........................................................................ Expectorant

USES:

• helps loosen phlegm (mucus) and thin bronchial secretions to rid the bronchial passageways of bothersome mucus and make coughs more productive
• temporarily relieves
o cough due to minor throat and bronchial irritation as may occur with the common cold or inhaled irritants
o the intensity of coughing
o the impulse to cough to help you get to sleep

Do not use

- for children under 12 year of age
- if you are now taking a prescription monoamine oxidase inhibitor (MAOI) (certain drugs for depression, psychiatric or emotional conditions or Parkinson’s disease), or for 2 weeks after stopping the MAOI drug. If you do not know if your prescription drug contains an MAOI, ask a doctor or pharmacist before taking this product.

Ask a doctor before use if you have

- persistent or chronic cough such as occurs with smoking, asthma, chronic bronchitis or emphysema
- cough accompanied by too much phlegm (mucus)

When using this product

- do not use more than directed

Stop use and ask a doctor if

cough lasts more than 7 days, comes back, or occurs with fever, rash, or persistent headache. These could be sign of serious illness.

PREGNANCY OR BREAST FEEDING

If pregnant or breast-feeding, ask a health professional before use.

KEEP OUT OF REACH OF CHILDREN. In case of accidental overdose, get medical help or contact a Poison Control Center (1-800-222-1222).

DIRECTIONS:

Adults and children 12 years of age and older: Take 1 tablet every 4 hours with a full glass of water. Do not exceed 6 doses in 24 hours.

Children under 12 years of age: Do not use

OTHER INFORMATION:

Store between 20ºC-25ºC (68ºF-77ºF).

- Keep in a dry place and do not expose to heat
- do not use if imprinted safety seal under cap is broken or missing.

INACTIVE INGREDIENTS:

microcrystalline cellulose, sodium starch glycolate, stearic acid powder, colloidal silicon dioxide, magnesium stearate, hypromellose, polyethylene glycol, D&C yellow

QUESTIONS OR COMMENTS?

Call (732) 698-5070 Monday through Friday 9 AM to 5 PM EST or www.pioneerlifesciences.com

This product is not manufactured or distributed by Reckitt Benckiser’s, owner of the registered trademark MUCINEX DM® Tablets.

Distributed by: GenCare Consumer Products, LLC 40E Cotters Ln, Suite A, East Brunswick, NJ 08816